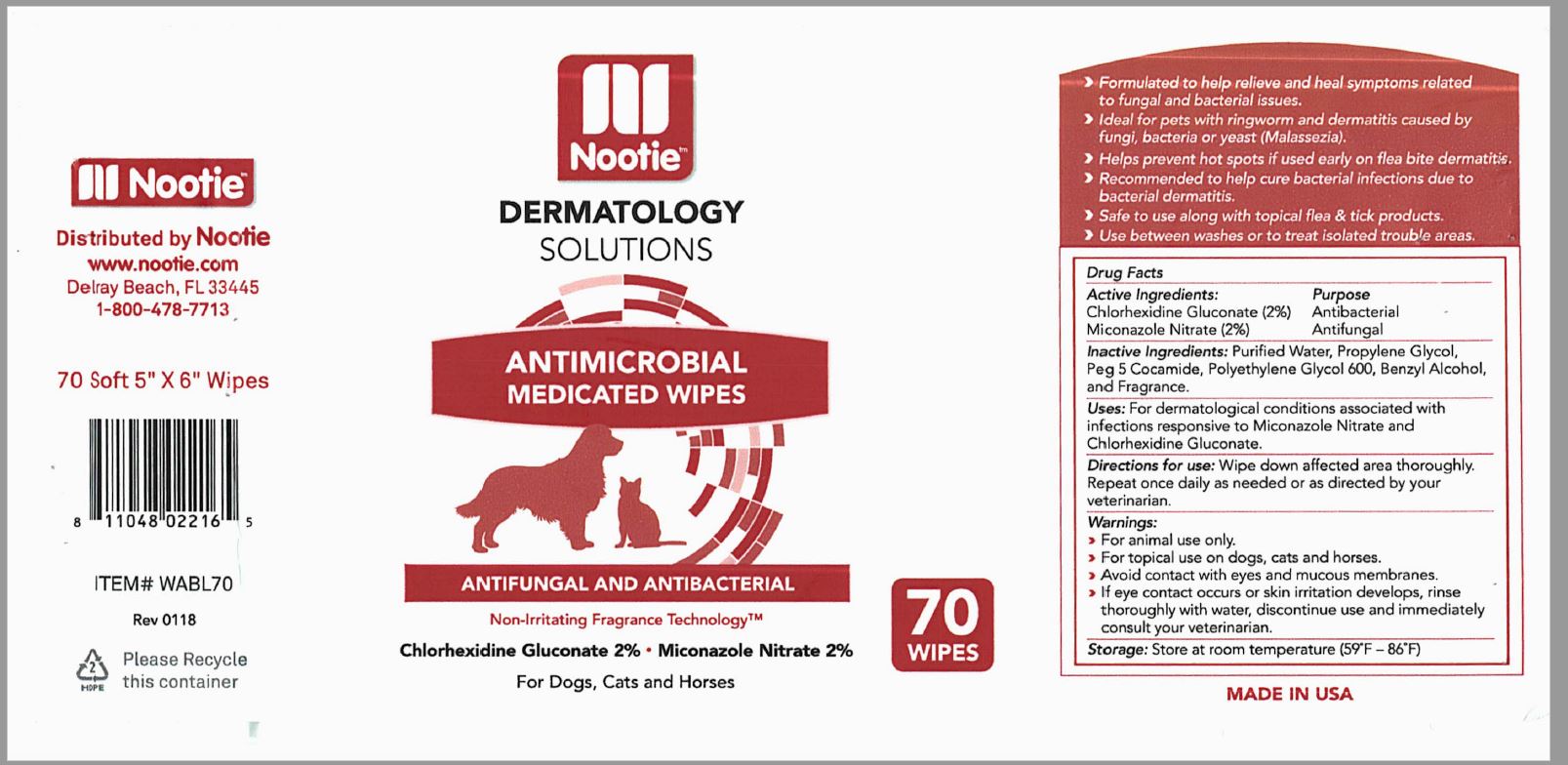 DRUG LABEL: Antimicrobial Wipes
NDC: 51437-205 | Form: SOLUTION
Manufacturer: Nootie
Category: animal | Type: OTC ANIMAL DRUG LABEL
Date: 20220207

ACTIVE INGREDIENTS: CHLORHEXIDINE GLUCONATE 3 mg/1 mL; MICONAZOLE 3 mg/1 mL
INACTIVE INGREDIENTS: WATER; PROPYLENE GLYCOL; PEG-5 COCAMINE; POLYETHYLENE GLYCOL 600; BENZYL ALCOHOL

Nootie - Dermatology Solutions - Antimicrobial Medicated Wipes (51437-205)

ACTIVE INGREDIENTS

Chlorhexidine Gluconate (2%)

Miconazole Nitrate (2%)

PURPOSE

ANTIBACTERIAL

ANTIFUNGAL

INACTIVE INGREDIENT

Purified Water, Propylene Glycol, Peg 5 cocamide, Benzyl Alcohol, and fragance.

Warnings

- For Animal Use Only
- For topical use on dogs and cats.
- Avoid contact with eyes and mucous membranes.
- If eye contact occurs or skin irritation develops, rinse thoroughly with water, discotinue use and immediately consult your veterinarian.

DOSAGE AND ADMINISTRATION

Directions for use

Apply to affected areas as directed by your veterinarian.

STORAGE AND HANDLING

Storage: Store at room temperature (59 °F- 86 °F)